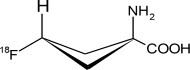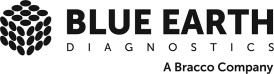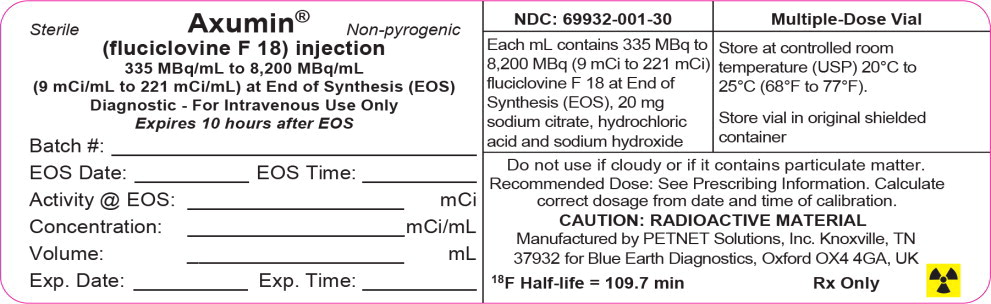 DRUG LABEL: Axumin
NDC: 69932-001 | Form: INJECTION, SOLUTION
Manufacturer: Blue Earth Diagnostics
Category: prescription | Type: HUMAN PRESCRIPTION DRUG LABEL
Date: 20250305

ACTIVE INGREDIENTS: FLUCICLOVINE F-18 221 mCi/1 mL
INACTIVE INGREDIENTS: SODIUM CITRATE, UNSPECIFIED FORM; HYDROCHLORIC ACID; SODIUM HYDROXIDE; WATER

HIGHLIGHTS OF PRESCRIBING INFORMATION

These highlights do not include all the information needed to use AXUMIN safely and effectively. See full prescribing information for AXUMIN.
AXUMIN (fluciclovine F 18) injection, for intravenous use
Initial U.S. Approval: 2016

1 INDICATIONS AND USAGE

Axumin is a radioactive diagnostic agent indicated for positron emission tomography (PET) imaging in men with suspected prostate cancer recurrence based on elevated blood prostate specific antigen (PSA) levels following prior treatment (1).

2 DOSAGE AND ADMINISTRATION

- Use appropriate radiation safety handling measures (2.1).
- Aseptically withdraw Axumin from its container and administer 370 MBq (10 mCi) as a bolus intravenous injection. (2.2).
- Initiate imaging 3 minutes to 5 minutes after administration. Scanning should start from mid-thigh and proceed to base of skull, with a total scan time of approximately 20 minutes to 30 minutes (2.4).
- The (radiation absorbed) effective dose associated with 370 MBq (10 mCi) of injected activity of Axumin is approximately 8 mSv (0.8 rem) in an adult (2.6).

3 DOSAGE FORMS AND STRENGTHS

Injection: clear, colorless solution in a 30 mL or 50 mL multiple-dose vial containing 335 MBq/mL to 8,200 MBq/mL (9 mCi/mL to 221 mCi/mL) fluciclovine F 18 at calibration time and date (3).

4 CONTRAINDICATIONS

None (4)

5 WARNINGS AND PRECAUTIONS

- Image interpretation errors can occur with Axumin imaging (5.1).
- Radiation risk: Axumin contributes to a patient's long-term cumulative radiation exposure. Ensure safe handling to protect patients and health care workers from unintentional radiation exposure (2.1, 5.3).

6 ADVERSE REACTIONS

Most commonly reported adverse reactions are injection site pain, erythema, and dysgeusia (6.1).

To report SUSPECTED ADVERSE REACTIONS, contact Blue Earth Diagnostics, Ltd at 1-855-AXUMIN1 (1-855-298-6461) or FDA at 1-800-FDA-1088 orwww.fda.gov/medwatch.

FULL PRESCRIBING INFORMATION

1 INDICATIONS AND USAGE

Axumin is indicated for positron emission tomography (PET) in men with suspected prostate cancer recurrence based on elevated blood prostate specific antigen (PSA) levels following prior treatment.

2 DOSAGE AND ADMINISTRATION

2.1 Radiation Safety - Drug Handling

Axumin is a radioactive drug and should be handled with appropriate safety measures to minimize radiation exposure during administration [see Warnings and Precautions (5.3) ]. Use waterproof gloves and effective shielding, including syringe shields, when handling and administering Axumin.

2.2 Recommended Dose and Administration Instructions

The recommended dose is 370 MBq (10 mCi) administered as an intravenous bolus injection.

- Inspect Axumin visually for particulate matter and discoloration before administration. Do not use the drug if the solution contains particulate matter or is discolored.
- Use aseptic technique and radiation shielding when withdrawing and administering Axumin.
- Calculate the necessary volume to administer based on calibration time and date, using a suitably calibrated instrument. The recommended maximum volume of injection of undiluted Axumin is 5mL.
- Axumin may be diluted with 0.9% Sodium Chloride Injection, USP.
- After the Axumin injection, administer an intravenous flush of sterile 0.9% Sodium Chloride Injection, USP to ensure full delivery of the dose.
- Dispose of any unused drug in a safe manner in compliance with applicable regulations.

2.3 Patient Preparation Prior to PET Imaging

- Advise the patient to avoid any significant exercise for at least one day prior to PET imaging.
- Advise patients not to eat or drink for at least 4 hours (other than sips of water for taking medications) prior to administration of Axumin.
- Advise patients to void approximately 30 minutes to 60 minutes prior to administration of Axumin and then refrain from voiding until after the scan has been completed

2.4 Image Acquisition Guidelines

Position the patient supine with arms above the head. Begin PET scanning 3 minutes to 5 minutes after completion of the Axumin injection. It is recommended that image acquisition should start from mid-thigh and proceed to the base of the skull. Typical total scan time is between 20 minutes to 30 minutes.

2.5 Image Display and Interpretation

Localization of prostate cancer recurrence in sites typical for prostate cancer recurrence is based on fluciclovine F 18 uptake in comparison with tissue background. For small lesions (less than 1cm in diameter) focal uptake greater than blood pool should be considered suspicious for prostate cancer recurrence. For larger lesions, uptake equal to or greater than bone marrow is considered suspicious for prostate cancer recurrence.

2.6 Radiation Dosimetry

The radiation absorbed doses estimated for adult patients following intravenous injection of Axumin are shown in Table 1. Values were calculated from human biodistribution data using OLINDA/EXM (Organ Level Internal Dose Assessment/Exponential Modeling) software.

The (radiation absorbed) effective dose resulting from the administration of the recommended activity of 370 MBq of Axumin is 8 mSv. For an administered activity of 370 MBq (10 mCi), the highest-magnitude radiation doses are delivered to the pancreas, cardiac wall, and uterine wall: 38 mGy, 19 mGy, and 17 mGy, respectively. If a CT scan is simultaneously performed as part of the PET procedure, exposure to ionizing radiation will increase in an amount dependent on the settings used in the CT acquisition.

Table 1: Estimated Radiation Absorbed Doses in Various Organs/Tissues in Adults who Received Axumin
Organ/Tissue | Mean Absorbed Dose per Unit Administered Activity (microGy/MBq)
Adrenal glands | 16
Brain | 9
Breasts | 14
Gallbladder wall | 17
Lower large intestine wall | 12
Small intestine wall | 13
Stomach wall | 14
Upper large intestine wall | 13
Heart wall | 52
Kidneys | 14
Liver | 33
Lungs | 34
Muscle | 11
Ovaries | 13
Pancreas | 102
Red bone marrow | 25
Osteogenic cells | 23
Skin | 8
Spleen | 24
Testes | 17
Thymus gland | 12
Thyroid | 10
Urinary bladder wall | 25
Uterus | 45
Total body | 13
Effective dose | 22 (microSv/MBq)

3 DOSAGE FORMS AND STRENGTHS

Injection: supplied as a clear, colorless solution in a 30 mL or 50 mL multiple-dose vial containing 335 MBq/mL to 8,200 MBq/mL (9 mCi/mL to 221 mCi/mL) fluciclovine F 18 at calibration time and date.

4 CONTRAINDICATIONS

None

5 WARNINGS AND PRECAUTIONS

5.1 Risk for Image Misinterpretation

Image interpretation errors can occur with Axumin PET imaging. A negative image does not rule out the presence of recurrent prostate cancer and a positive image does not confirm the presence of recurrent prostate cancer. The performance of Axumin seems to be affected by PSA levels [See Clinical Studies (14)] . Fluciclovine F 18 uptake is not specific for prostate cancer and may occur with other types of cancer and benign prostatic hypertrophy in primary prostate cancer. Clinical correlation, which may include histopathological evaluation of the suspected recurrence site, is recommended.

5.2 Hypersensitivity Reactions

Hypersensitivity reactions including anaphylaxis may occur in patients who receive Axumin. Emergency resuscitation equipment and personnel should be immediately available.

5.3 Radiation Risks

Axumin use contributes to a patient's overall long-term cumulative radiation exposure. Long-term cumulative radiation exposure is associated with an increased risk for cancer. Ensure safe handling to minimize radiation exposure to the patient and health care providers [see Dosage and Administration (2.1)] .

6 ADVERSE REACTIONS

Clinical Trials Experience

Because clinical trials are conducted under widely varying conditions, adverse reaction rates observed in the clinical trials of a drug cannot be directly compared to rates in the clinical trials of another drug and may not reflect the rates observed in practice. The clinical trial database for Axumin includes data from 877 subjects including 797 males diagnosed with prostate cancer. Most patients received a single administration of Axumin, a small number of subjects (n = 50) received up to five administrations of the drug. The mean administered activity was 370 MBq (range, 163 MBq to 485 MBq).

Adverse reactions were reported in ≤1% of subjects during clinical studies with Axumin. The most common adverse reactions were injection site pain, injection site erythema and dysgeusia.

8 USE IN SPECIFIC POPULATIONS

8.1 Pregnancy

Risk Summary

Axumin is not indicated for use in females and there is no information on the risk of adverse development outcomes in pregnant women or animals with the use of fluciclovine F 18.

8.2 Lactation

Risk Summary

Axumin is not indicated for use in females and there is no information of the presence of fluciclovine F 18 in human milk.

8.3 Pediatric Use

Safety and effectiveness have not been established in pediatric patients.

8.4 Geriatric Use

Of the total number of patients in clinical studies of Axumin, the average age was 66 years with a range of 21 to 90 years. No overall differences in safety or effectiveness were observed between older subjects and younger subjects.

10 OVERDOSAGE

In case of overdose of Axumin, encourage patients to maintain hydration and to void frequently to minimize radiation exposure.

11 DESCRIPTION

11.1 Chemical Characteristics

Axumin contains the fluorine 18 (F 18) labeled synthetic amino acid analog fluciclovine. Fluciclovine F 18 is a radioactive diagnostic agent used with PET imaging. Chemically, fluciclovine F 18 is (1r, 3r)-1-amino-3[^18F]fluorocyclobutane-1-carboxylic acid. The molecular weight is 132.1 and the structural formula is:

Axumin is a sterile, non-pyrogenic, clear, colorless, hyperosmolal (approximately 500 mOsm/kg to 540 mOsm/kg) injection for intravenous use. Each milliliter contains up to 2 micrograms of fluciclovine, 335 MBq to 8,200 MBq (9 mCi to 221 mCi) fluciclovine F 18 at calibration time and date, and 20 mg trisodium citrate in water for injection. The solution also contains hydrochloric acid, sodium hydroxide and has a pH between 4 and 6.

11.2 Physical Characteristics

Fluorine 18 (F 18) is a cyclotron produced radionuclide that decays by positron emission (ß+ decay, 96.7%) and orbital electron capture (3.3%) to stable oxygen 18 with a physical half-life of 109.7 minutes. The positron can undergo annihilation with an electron to produce two gamma rays; the energy of each gamma ray is 511 keV (Table 2).

Table 2: Principal Radiation Produced from Decay of Fluorine 18 Radiation
 | Energy (keV) | Abundance (%)
Positron | 249.8 | 96.7
Gamma | 511.0 | 193.5

11.3 External Radiation

The point source air-kerma coefficient for F 18 is 3.75 x 10^-17Gy m^2/(Bq s). The first half-value thickness of lead (Pb) for F 18 gamma rays is approximately 6 mm. The relative reduction of radiation emitted by F 18 that results from various thicknesses of lead shielding is shown in Table 3. The use of 8 cm of Pb will decrease the radiation transmission (i.e., exposure) by a factor of about 10,000.

Table 3: Radiation Attenuation of 511 keV Gamma Rays by Lead Shielding
Shield Thickness cm of Lead (Pb) | Coefficient of Attenuation
0.6 | 0.5
2 | 0.1
4 | 0.01
6 | 0.001
8 | 0.0001

12 CLINICAL PHARMACOLOGY

12.1 Mechanism of action

Fluciclovine F 18 is a synthetic amino acid transported across mammalian cell membranes by amino acid transporters, such as LAT-1 and ASCT2, which are upregulated in prostate cancer cells. Fluciclovine F 18 is taken up to a greater extent in prostate cancer cells compared with surrounding normal tissues.

12.2 Pharmacodynamics

Following intravenous administration, the tumor-to-normal tissue contrast is highest between 4 and 10 minutes after injection, with a 61% reduction in mean tumor uptake at 90 minutes after injection.

12.3 Pharmacokinetics

Distribution

Following intravenous administration, fluciclovine F 18 distributes to the liver (14% of administered activity), pancreas (3%), lung (7%), red bone marrow (12%) and myocardium (4%). With increasing time, fluciclovine F 18 distributes to skeletal muscle.

Excretion

Across the first four hours post-injection, 3% of administered radioactivity was excreted in the urine. Across the first 24 hours post-injection, 5% of administered radioactivity was excreted in the urine.

13 NONCLINICAL TOXICOLOGY

13.1 Carcinogenesis, Mutagenesis, Impairment of Fertility

Carcinogenesis

No long term studies in animals have been performed to evaluate the carcinogenic potential of fluciclovine.

Mutagenesis

Fluciclovine was not mutagenic in vitroin reverse mutation assay in bacterial cells and in chromosome aberration test in cultured mammalian cells, and was negative in an in vivoclastogenicity assay in rats after intravenous injection of doses up to 43 mcg/kg. However, fluciclovine F 18 has the potential to be mutagenic because of the F 18 radioisotope.

Impairment of Fertility

No studies in animals have been performed to evaluate potential impairment of fertility in males or females.

14 CLINICAL STUDIES

The safety and efficacy of Axumin were evaluated in two studies (Study 1 and Study 2) in men with suspected recurrence of prostate cancer based on rising PSA levels following radical prostatectomy and/or radiotherapy.

Study 1 evaluated 105 Axumin scans in comparison to histopathology obtained by biopsy of the prostate bed and biopsies of lesions suspicious by imaging. PET/CT imaging generally included the abdomen and pelvic regions. The Axumin images were originally read by on-site readers. The images were subsequently read by three blinded independent readers. Table 4shows the performance of Axumin in the detection of recurrence in each patient scan and, specifically, within the prostatic bed and extra-prostatic regions, respectively. The results of the independent read were generally consistent with one another and confirmed the results of the on-site reads.

Table 4: Performance of Axumin in Patients with Biochemically Suspected Recurrent Prostate Cancer, at the Patient Level and at the Prostate Bed and Extraprostatic Region Levels
 | Reader 1 | Reader 2 | Reader 3
Patient | N = 104 | N = 105 | N = 99
True Positive | 75 | 72 | 63
False Positive | 24 | 23 | 13
True Negative | 5 | 7 | 15
False Negative | 0 | 3 | 8
Prostate Bed | N = 98 | N = 97 | N = 96
True Positive | 58 | 56 | 47
False Positive | 29 | 26 | 15
True Negative | 10 | 12 | 24
False Negative | 1 | 3 | 10
Extraprostatic | N = 28 | N = 28 | N = 25
True Positive | 25 | 26 | 22
False Positive | 2 | 2 | 2
True Negative | 0 | 0 | 0
False Negative | 1 | 0 | 1
N = number of patient scans evaluated

The detection rate of Axumin seems to be affected by PSA levels [see Warnings and Precautions (5.1)] . In general, patients with negative scans had lower PSA values than those with positive scans. The detection rate (number with positive scans/total scanned) for patients with a PSA value of less than or equal to 1.78 ng/mL (1st PSA quartile) was 15/25, of which 11 were histologically confirmed as positive. In the remaining three PSA quartiles, the detection rate was 71/74, of which 58 were histologically confirmed. Among the 25 patients in the first PSA quartile, there were 4 false positive scans and 1 false negative scan. For the 74 patients with PSA levels greater than1.78 ng/mL, there were 13 false positive scans and no false negative scans.

Study 2 evaluated the concordance between 96 Axumin and C11 choline scans in patients with median PSA value of 1.44 ng/mL (interquartile range = 0.78 ng/mL to 2.8 ng/mL). The C 11 choline scans were read by on-site readers. The Axumin scans were read by the same three blinded independent readers used for Study 1. The agreement values between the Axumin and C11 choline reads were 61%, 67% and 77%, respectively.

16 HOW SUPPLIED/STORAGE AND HANDLING

16.1 How Supplied

Axumin is supplied as a clear, colorless injection in a 30 mL or 50 mL multiple-dose glass vial containing approximately 26 mL solution of 335 MBq/mL to 8,200 MBq/mL (9 mCi/mL to 221 mCi/mL) fluciclovine F 18 at calibration time and date.

30 mL sterile multiple-dose vial: NDC 69932-001-30

50 mL sterile multiple-dose vial: NDC 69932-001-50

16.2 Storage and Handling

Store Axumin at controlled room temperature (USP) 20°C to 25°C (68°F to 77°F). Axumin does not contain a preservative. Store Axumin within the original container in radiation shielding. Do not use Axumin more than 10 hours after end of synthesis and dispose of in accordance with institutional guidelines.

This preparation is approved for use by persons under license by the Nuclear Regulatory Commission or the relevant regulatory authority of an Agreement State.

17 PATIENT COUNSELING INFORMATION

- Instruct patients to avoid significant exercise for at least a day before the PET scan.
- Instruct patients not to eat or drink for at least 4 hours before the PET scan (other than sips of water for taking medications).
- Instruct patients to try to urinate approximately 30 minutes to 60 minutes prior to planned start time of the PET scan and to avoid further urination until after the scan has been completed.

Marketed by Blue Earth Diagnostics Ltd. Oxford, UK OX4 4GA
Axumin®is a registered trademark of Blue Earth Diagnostics Ltd.
© 2022 Blue Earth Diagnostics Ltd – all rights reserved.

PACKAGE LABEL

Principal Display Panel - 30 mL Multiple-Dose Vial Label

Sterile

Axumin™

Non-pyrogenic

335 MBq/mL to 8,200 MBq/mL (9 mCi/mL to
221 mCi/mL) at End of Synthesis (EOS)

Diagnostic - For Intravenous Use Only

Expires 10 hours after EOS

Batch #: ________________________________

EOS Date: __________ EOS Time: __________

Activity @ EOS: ___________________ mCi

Concentration: ___________________ mCi/mL

Volume: ___________________ mL

Exp. Date: __________ Exp. Time: __________